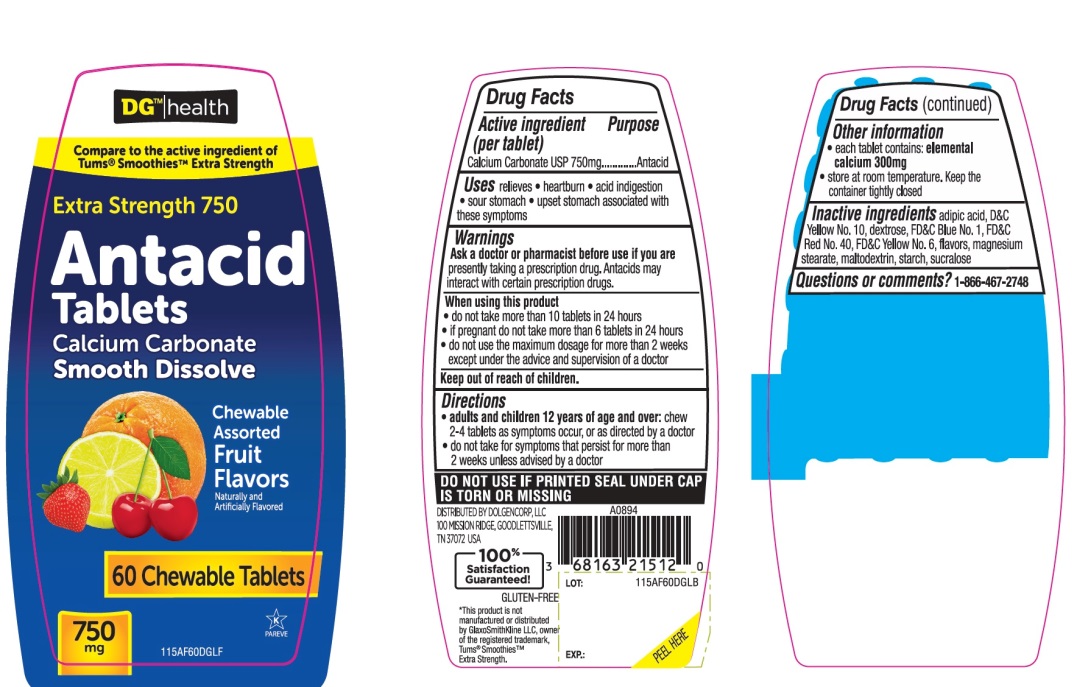 DRUG LABEL: DG health Extra Strength

NDC: 55910-605 | Form: TABLET, CHEWABLE
Manufacturer: DOLGENCORP, LLC
Category: otc | Type: HUMAN OTC DRUG LABEL
Date: 20250822

ACTIVE INGREDIENTS: CALCIUM CARBONATE 750 mg/1 1
INACTIVE INGREDIENTS: ADIPIC ACID; D&C YELLOW NO. 10; DEXTROSE, UNSPECIFIED FORM; FD&C BLUE NO. 1; FD&C RED NO. 40; FD&C YELLOW NO. 6; MAGNESIUM STEARATE; MALTODEXTRIN; STARCH, CORN; SUCRALOSE

DG health Extra Strength Smooth Dissolve Antacid Assorted Fruit 60 Chewable Tablets

Active ingredient (per tablet)

Calcium Carbonate 750 mg

Purpose

Antacid

Uses

relieves:

- heartburn
- acid indigestion
- sour stomach
- upset stomach associated with these symptoms

Ask a doctor or pharmacist before use if you are

- presently taking a prescription drug. Antacids may interact with certain prescription drugs.

When using this product

- do not take more than 10 tablets in a 24-hours
- if pregnant do not take more than 6 tablets in 24 hours
- do not use the maximum dosage for more than 2 weeks except under the advice and supervision of a doctor.

Directions

- adults and children 12 years of age and over:chew 2-4 tablets as symptoms occur, or as directed by a doctor.
- do not take for symptoms that persists for more than 2 weeks unless advised by a doctor

Other information

- each tablet contains : elemental calcium 300 mg
- store at room temperature. Keep the container tightly closed.

DO NOT USE IF PRINTED SEAL UNDER CAP IS TORN OR MISSING

Inactive ingredients

adipic acid, D&C Yellow No. 10, dextrose, FD&C Blue No. 1, FD&C Red No. 40, FD&C Yellow No. 6, flavors, magnesium stearate, maltodextrin, starch, sucralose.

Questions or comments

1-866-467-2748

PRINCIPAL DISPLAY PANEL

DG™ health

NDC 55910-605-60

Compare to the active ingredient of Tums®Smoothies™ Extra Strength

EXTRA STRENGTH 750

Antacid Tablets

Calcium Carbonate

Smooth Dissolve
Chewable Assorted Fruit Flavors

Naturally and Artificially Flavored

60 Chewable Tablets

750 mg

K PAREVE

GLUTEN-FREE
DISTRIBUTED BY DOLGENCORP, LLC

100 MISSION RIDGE, GOODLETTSVILLE,

TN 37072 USA

100% Satisfaction Guaranteed

*This product is not manufactured or distributed by GlaxoSmithKline LLC, owner of the registered trademark, Tums® Smoothies™ Extra Strength.